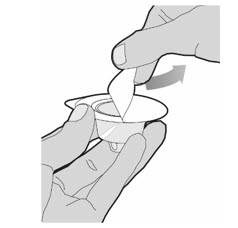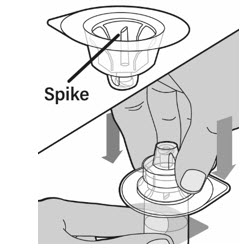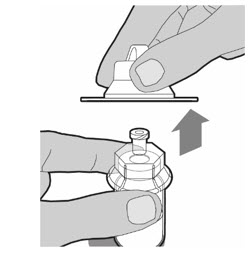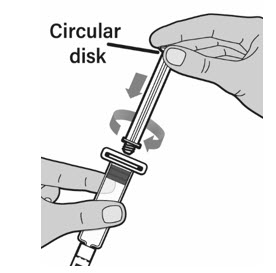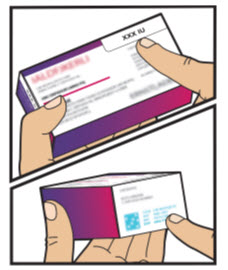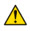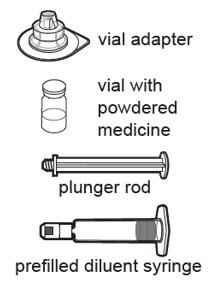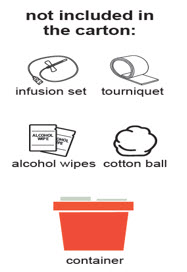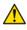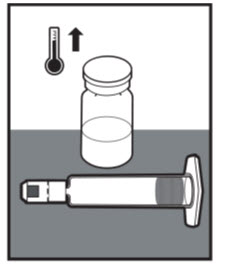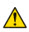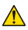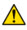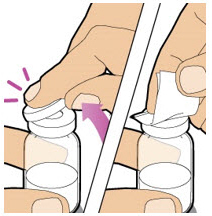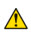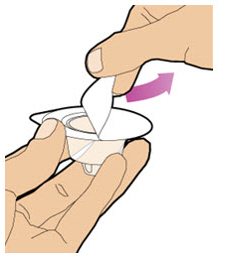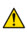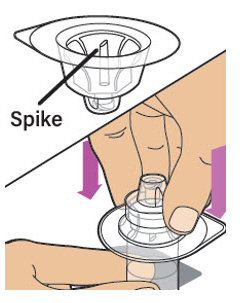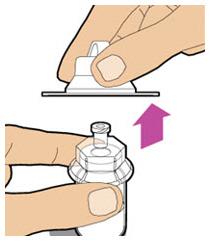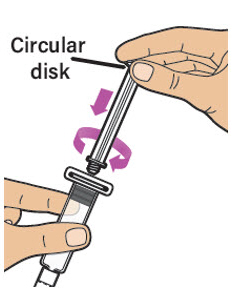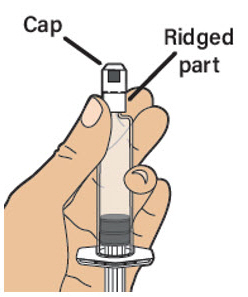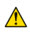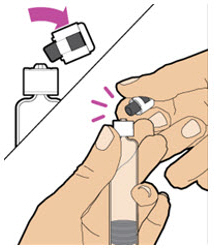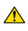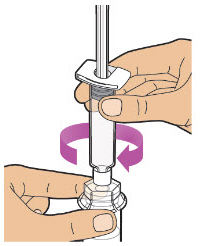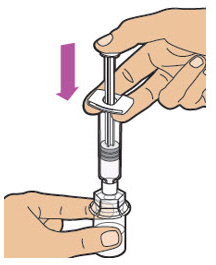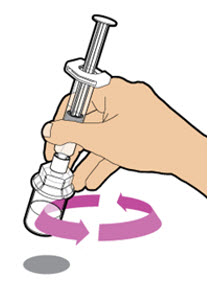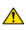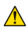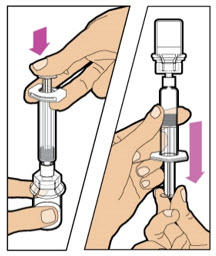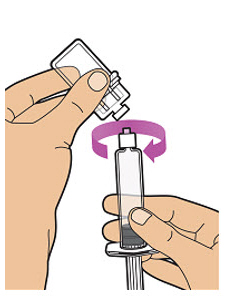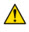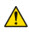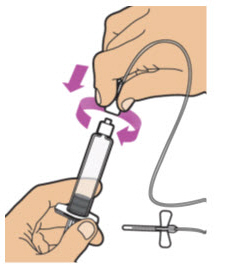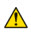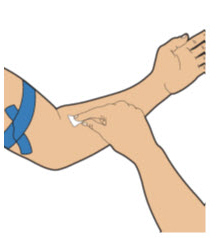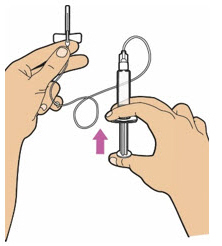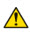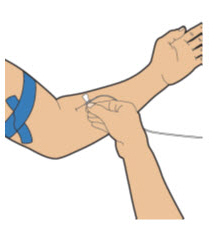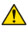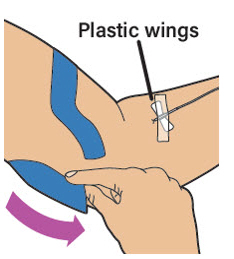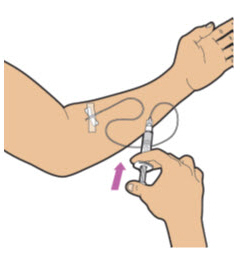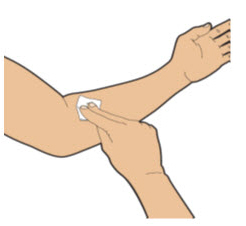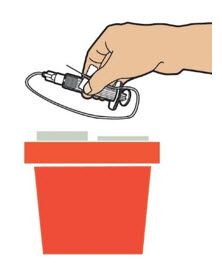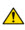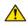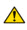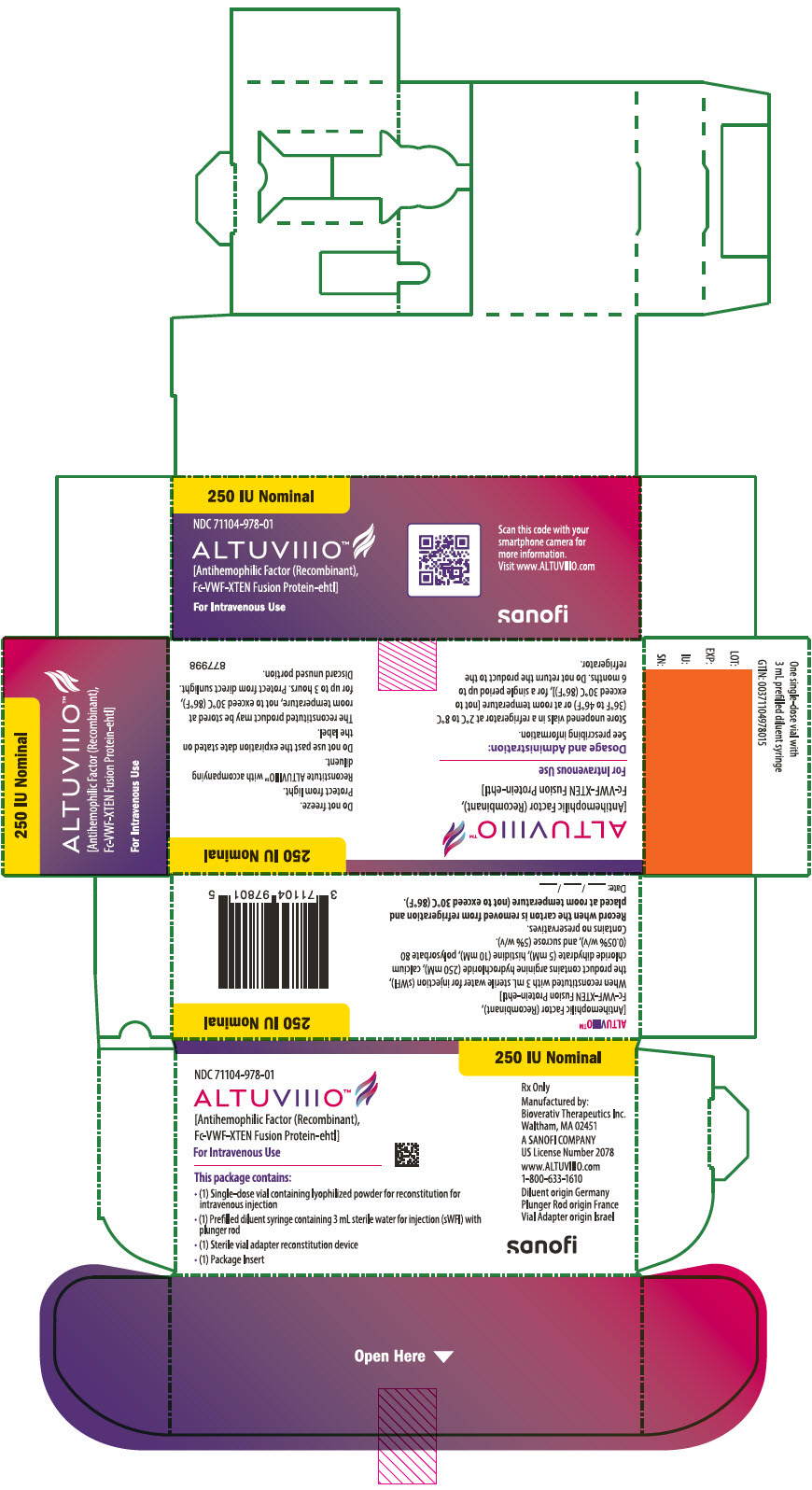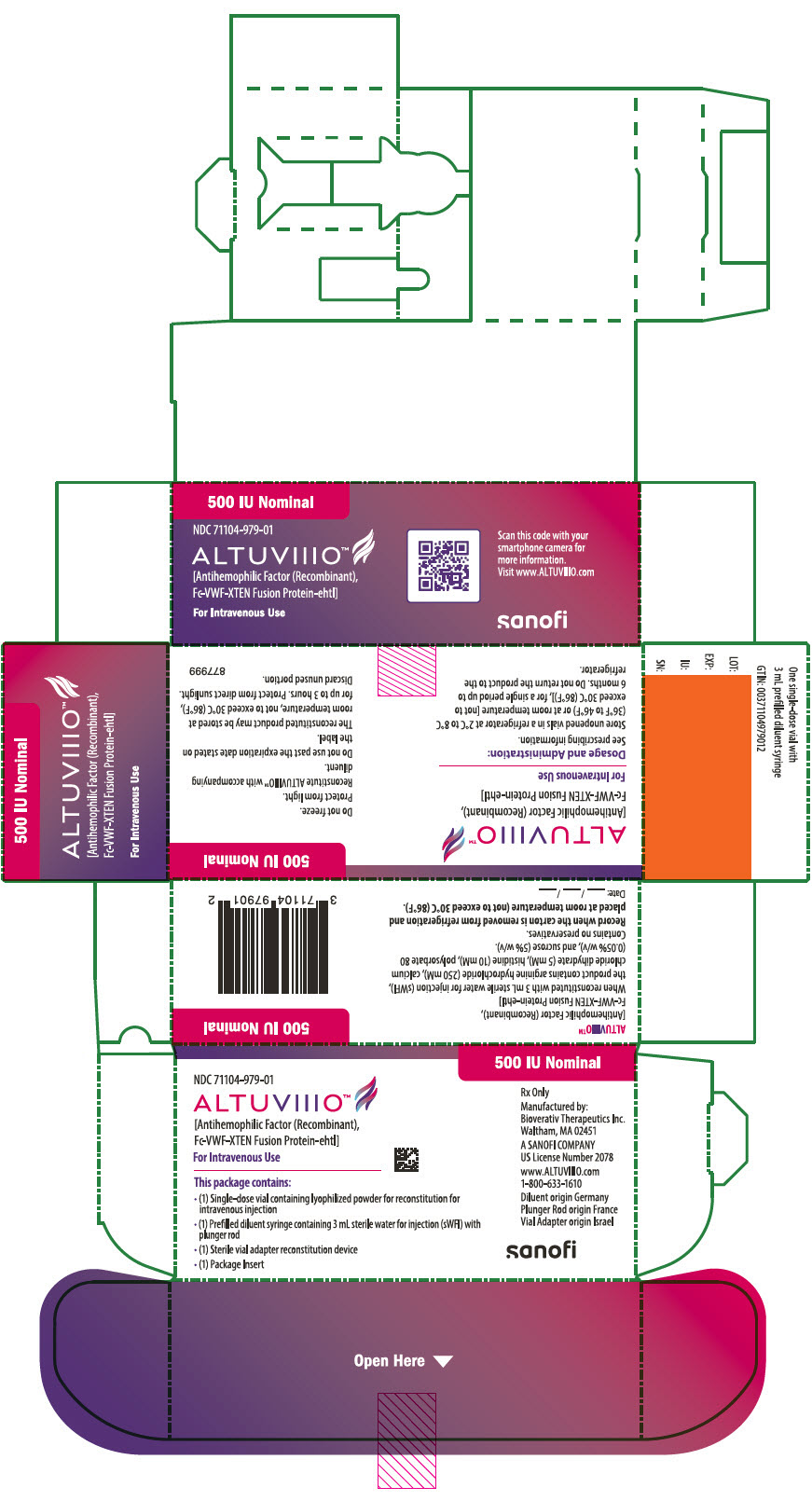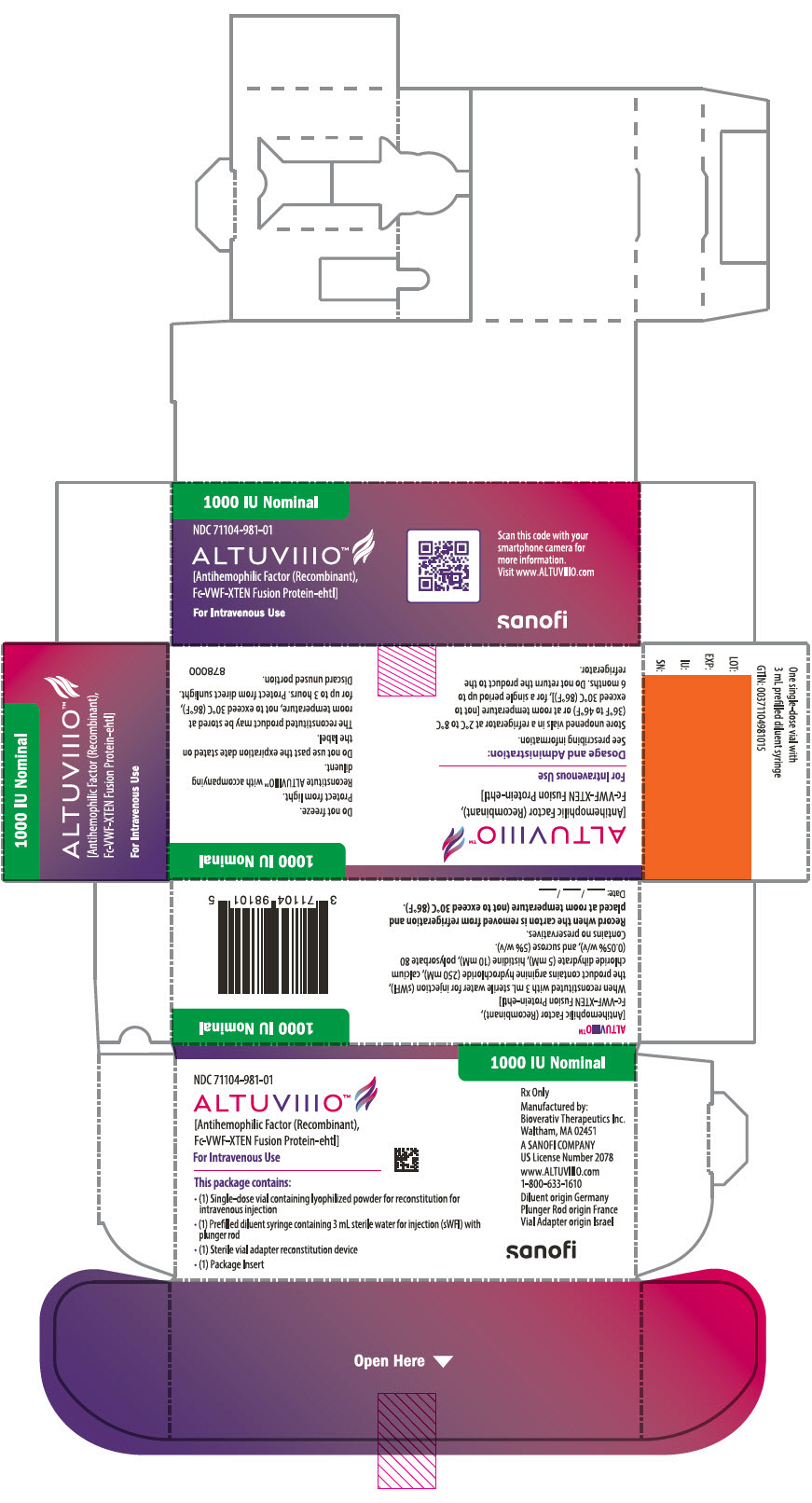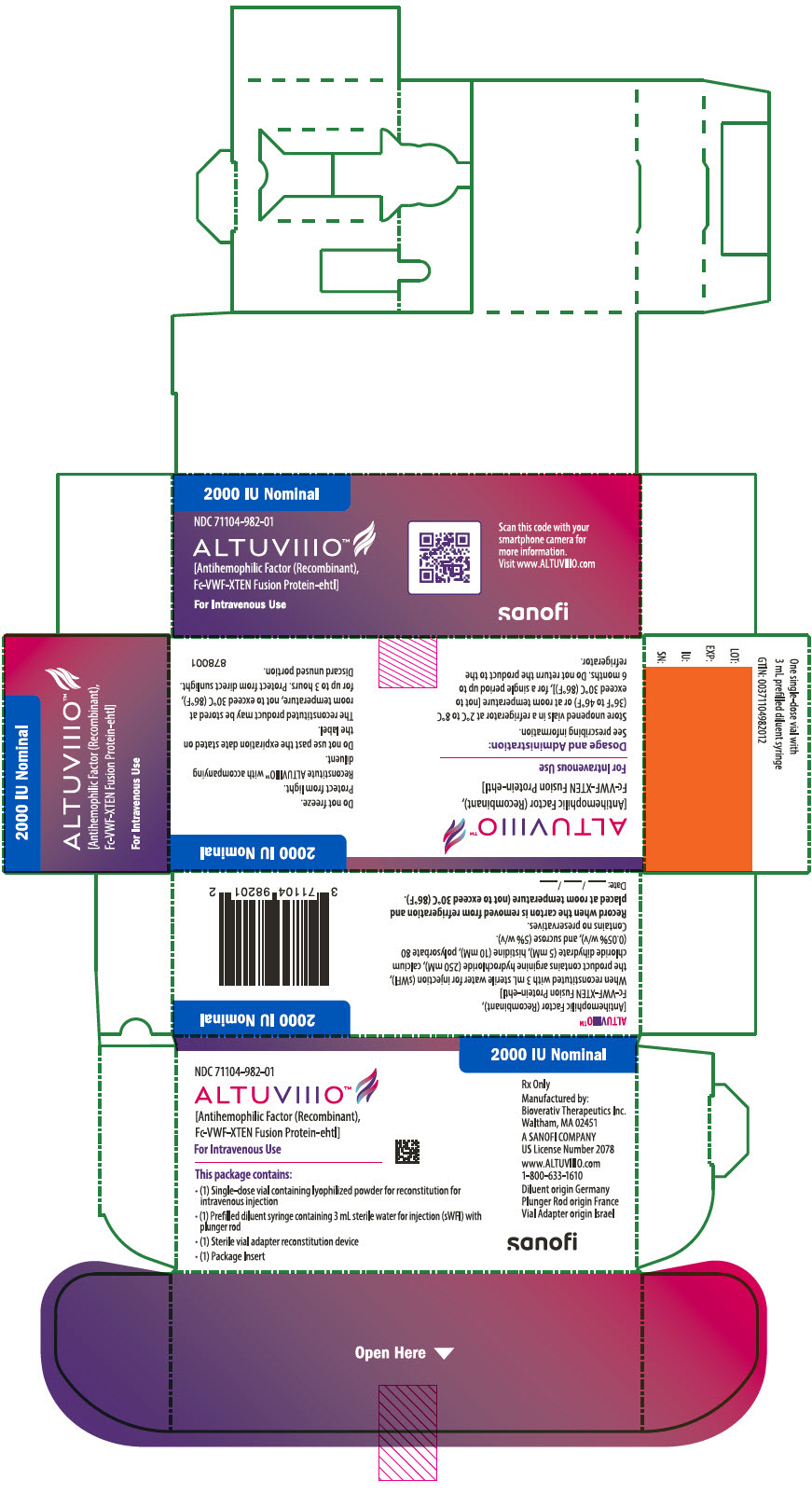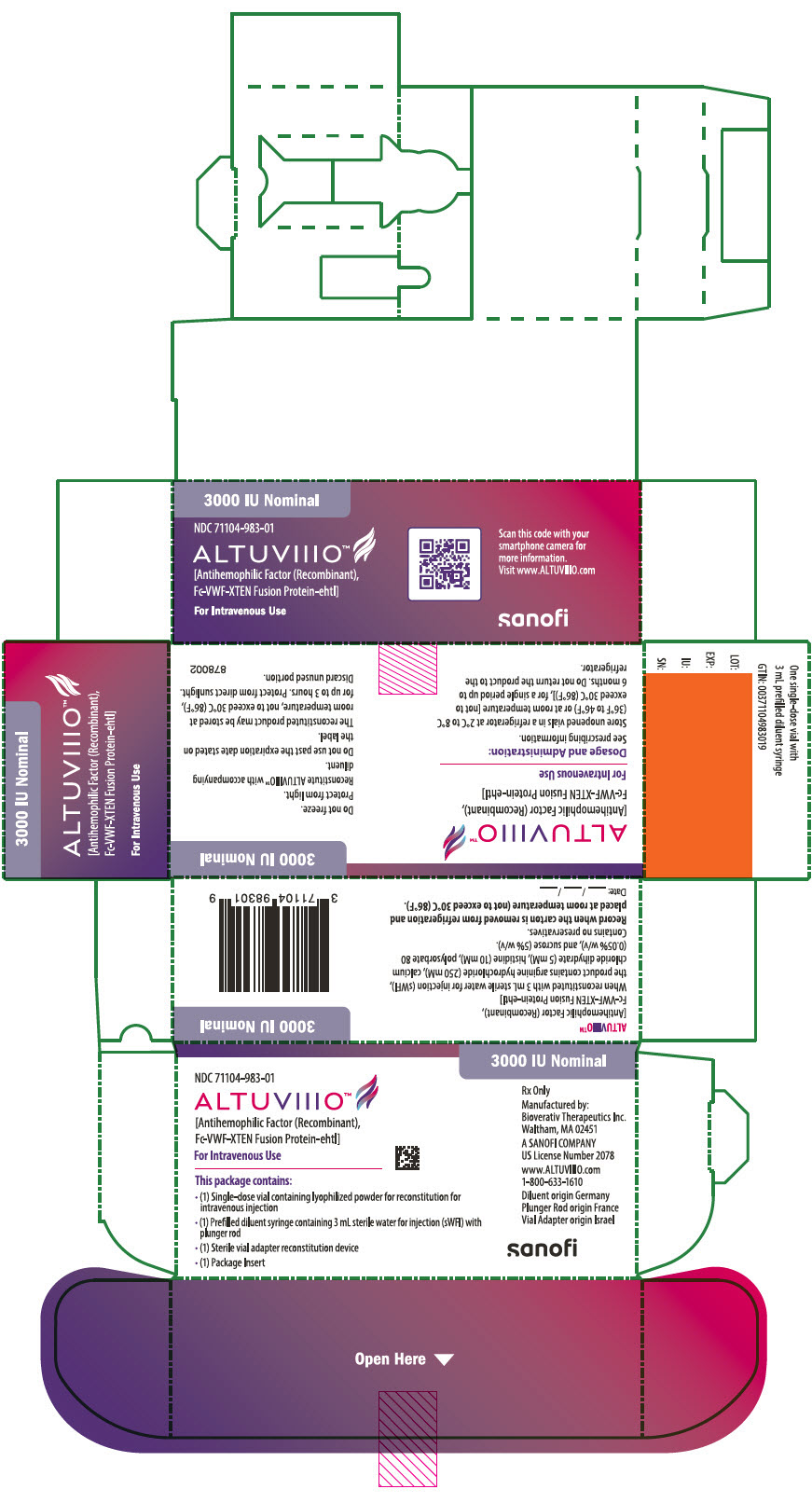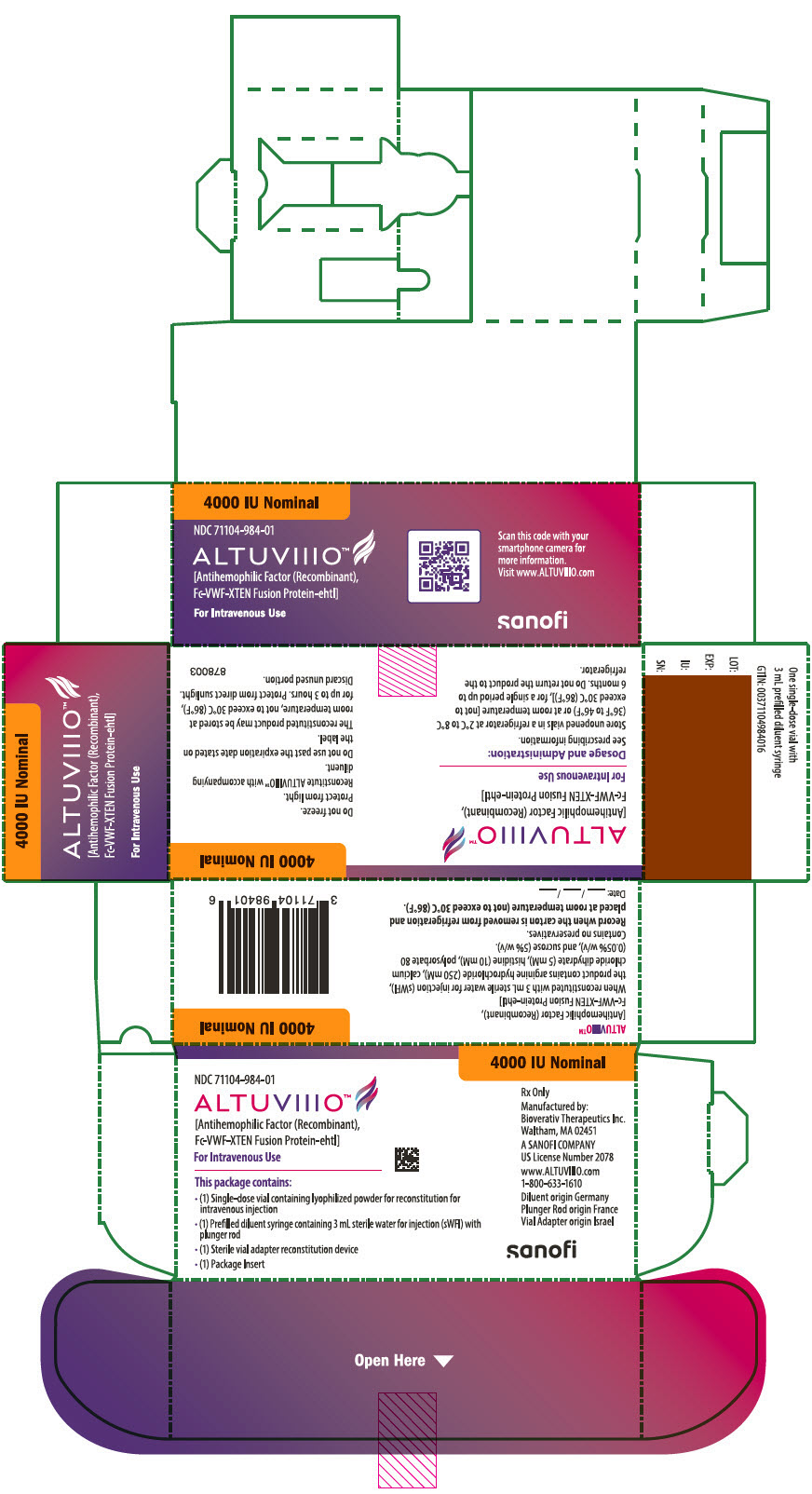 DRUG LABEL: ALTUVIIIO
NDC: 71104-978 | Form: KIT | Route: INTRAVENOUS
Manufacturer: Bioverativ Therapeutics Inc.
Category: prescription | Type: HUMAN PRESCRIPTION DRUG LABEL
Date: 20260223

ACTIVE INGREDIENTS: EFANESOCTOCOG ALFA 250 [iU]/3 mL
INACTIVE INGREDIENTS: ARGININE HYDROCHLORIDE; CALCIUM CHLORIDE; HISTIDINE; POLYSORBATE 80; SUCROSE; WATER

HIGHLIGHTS OF PRESCRIBING INFORMATION

These highlights do not include all the information needed to use ALTUVIIIO® safely and effectively. See full prescribing information for ALTUVIIIO.
ALTUVIIIO [antihemophilic factor (recombinant), Fc-VWF-XTEN fusion protein-ehtl], lyophilized powder for solution, for intravenous use
Initial U.S. Approval: 2023

RECENT MAJOR CHANGES

Warnings and Precautions (5.2) | 12/2025

1 INDICATIONS AND USAGE

ALTUVIIIO [antihemophilic factor (recombinant), Fc-VWF-XTEN fusion protein-ehtl] is a recombinant DNA-derived, Factor VIII concentrate indicated for use in adults and children with hemophilia A (congenital factor VIII deficiency) for:

- Routine prophylaxis to reduce the frequency of bleeding episodes
- On-demand treatment & control of bleeding episodes
- Perioperative management of bleeding (1)

Limitation of Use:
ALTUVIIIO is not indicated for the treatment of von Willebrand disease. (1)

2 DOSAGE AND ADMINISTRATION

For intravenous use only.

- Each ALTUVIIIO vial label states Factor VIII activity in international units (IU or unit). (2.1)
- For routine prophylaxis: 50 IU/kg once weekly. (2.1)
- For on-demand treatment and control of bleeding episodes and perioperative management: 50 IU/kg (2.1)
  Estimated Increment of Factor VIII (IU/dL or % of normal) = 50 IU/kg × 2 (IU/dL per IU/kg) (2.1)

To achieve a specific target Factor VIII activity level, use the following formula: Dosage (IU) = Body Weight (kg) × Desired Factor VIII Increase (IU/dL or % normal) × 0.5 (IU/kg per IU/dL). (2.1)

3 DOSAGE FORMS AND STRENGTHS

For injection: nominally 250, 500, 750, 1000, 2000, 3000, or 4000 IU, lyophilized powder in single-dose vials for reconstitution. (3)

4 CONTRAINDICATIONS

Do not use in patients who have had severe hypersensitivity reactions, including anaphylaxis, to ALTUVIIIO or excipients of ALTUVIIIO. (4)

5 WARNINGS AND PRECAUTIONS

- Hypersensitivity reactions, including anaphylaxis, have occurred with ALTUVIIIO. If symptoms occur, immediately discontinue ALTUVIIIO and initiate appropriate treatment. (5.1)
- Neutralizing antibodies (inhibitors) to Factor VIII have been reported. If expected plasma Factor VIII activity levels are not attained, or if bleeding is not controlled with an appropriate dose, perform an assay that measures Factor VIII inhibitor concentration. (5.2, 5.3)

6 ADVERSE REACTIONS

Most common adverse reactions (incidence >10%) are headache and arthralgia. (6.1)

To report SUSPECTED ADVERSE REACTIONS, contact Bioverativ Therapeutics Inc. (A SANOFI COMPANY) at 1-800-633-1610 or FDA at 1-800-FDA-1088 or www.fda.gov/medwatch.

8 USE IN SPECIFIC POPULATIONS

Pediatric Use: No dosing adjustment is needed in this population. (8.4)

FULL PRESCRIBING INFORMATION

1 INDICATIONS AND USAGE

ALTUVIIIO is indicated for use in adults and pediatric patients with hemophilia A (congenital factor VIII deficiency) for:

- Routine prophylaxis to reduce the frequency of bleeding episodes
- On-demand treatment and control of bleeding episodes
- Perioperative management of bleeding

Limitation of Use

ALTUVIIIO is not indicated for the treatment of von Willebrand disease.

2 DOSAGE AND ADMINISTRATION

For intravenous use after reconstitution only.

2.1 Dose

- Each ALTUVIIIO vial label states the Factor VIII potency in international units (IU). One IU corresponds to the Factor VIII activity contained in one milliliter of normal human plasma, as defined by the current World Health Organization (WHO) international standard for Factor VIII concentrate.
- Potency assignment for ALTUVIIIO is determined using an activated partial thromboplastin time (aPTT)-based one-stage clotting assay. It is recommended to use a validated one-stage clotting assay to measure ALTUVIIIO Factor VIII activity in plasma. The ALTUVIIIO Factor VIII activity level is overestimated by the chromogenic assay and a specific ellagic acid based aPTT reagent in one-stage clotting assay by approximately 2.5-fold [see Warnings and Precautions (5.3)].

For the dose of 50 IU/kg, the expected in vivo peak increase in Factor VIII level expressed as IU/dL (or % of normal) is estimated using the following formula:

Estimated Increment of Factor VIII (IU/dL or % of normal) = 50 IU/kg × 2 (IU/dL per IU/kg)

To achieve a specific target Factor VIII activity level, use the following formula: Dosage (IU) = Body Weight (kg) × Desired Factor VIII Increase (IU/dL or % normal) × 0.5 (IU/kg per IU/dL).

Routine Prophylaxis

The recommended dosing for routine prophylaxis for adults and children is 50 IU/kg of ALTUVIIIO administered once weekly.

On-demand Treatment and Control of Bleeding Episodes

ALTUVIIIO dosing for the on-demand treatment and control of bleeding episodes is provided in Table 1.

Table 1: Dosing for On-demand Treatment and Control of Bleeding Episodes
Type of Bleeding | Recommended Dose | Additional Information
Minor and Moderate For example: Uncomplicated joint bleeds, minor muscular bleeds, mucosal or subcutaneous bleeds | Single dose of 50 IU/kg | For minor and moderate bleeding episodes occurring within 2 to 3 days after a prophylactic dose, a lower dose of 30 IU/kg dose may be used. Additional doses of 30 or 50 IU/kg every 2 to 3 days may be considered.
Major For example: Intracranial, retroperitoneal, iliopsoas and neck bleeds, muscle bleeds with compartment syndrome and bleeds associated with a significant decrease in the hemoglobin level | Single dose of 50 IU/kg | Additional doses of 30 or 50 IU/kg every 2 to 3 days can be considered.

For resumption of prophylaxis (if applicable) after treatment of a bleed, it is recommended to allow an interval of at least 72 hours between the last 50 IU/kg dose for treatment of a bleed and resuming prophylaxis dosing. Thereafter, prophylaxis can be continued as usual on the patient's regular schedule.

Perioperative Management

ALTUVIIIO dosing for perioperative management is provided in Table 2.

Table 2: Dosing for Perioperative Management
Type of Surgery | Pre-operative Dose | Post-operative Dose
Minor For example: Tooth extraction | Single dose of 50 IU/kg | An additional dose of 30 or 50 IU/kg after 2 to 3 days may be considered.
Major For example: Intracranial, intra-abdominal, joint replacement surgery, or complicated dental procedures. | Single dose of 50 IU/kg | Additional doses of 30 or 50 IU/kg every 2 to 3 days may be administered as clinically needed for perioperative management.

2.2 Preparation and Reconstitution

1. Use aseptic technique and a flat work surface during the reconstitution procedure.
2. Allow the ALTUVIIIO vial, containing the white to off-white lyophilized powder, and the prefilled diluent syringe to reach room temperature before use.
3. Remove the plastic cap from the ALTUVIIIO vial and wipe the rubber stopper of the vial with an alcohol wipe. Allow the rubber stopper to dry.
4. Completely remove the backing from the vial adapter package by peeling back the lid. Do not remove the vial adapter from the package or touch the inside of the package of the adapter.
5. Keep the vial on a flat surface. Hold the vial with one hand and using the other hand, place the vial adapter in its package over the vial. The spike should be placed directly above the center of the rubber stopper. Push the vial adapter straight down until the spike on the vial adapter punctures the center of the vial stopper and is fully inserted.
6. Lift the package cover away from the vial adapter and throw away the cover.
7. Only use the prefilled diluent syringe provided to reconstitute the powdered medicine. Hold the plunger rod by the circular disk. Place the tip of the plunger rod into the end of the prefilled diluent syringe. Turn the plunger rod to the right until it is firmly attached.
8. With one hand, hold the prefilled diluent syringe directly under the cap with the cap pointing up. Make sure you are holding the prefilled diluent syringe by the ridged part directly under the cap. Do not use if the cap has been removed or is not securely attached.
9. With your other hand, grasp the cap and bend it at a 90 degree angle until it snaps off. After the cap snaps off, you will see the glass tip of the prefilled diluent syringe. Do not touch the glass tip of the prefilled diluent syringe or the inside of the cap.
10. Be sure the vial is sitting on a flat surface. Insert the tip of the prefilled diluent syringe into the vial adapter opening. Turn the prefilled diluent syringe to the right until it is securely attached to the vial adapter.
11. Slowly push down on the plunger rod to inject all of the liquid (diluent) from the prefilled diluent syringe into the vial. The plunger rod may rise slightly afterward. This is normal.
12. With the prefilled diluent syringe still connected to the adapter, gently swirl the vial until the powder is completely dissolved. Check the solution through the vial to make sure the powder is fully dissolved. The solution should look clear and colorless to opalescent. Do not shake. Do not use the reconstituted ALTUVIIIO if it contains visible particles or is cloudy.
  POOLING: pooling is the process of combining two or more reconstituted vials into a larger luer lock syringe (not provided in the carton). If the dose requires more than one vial, reconstitute each vial as described above (See Steps 3–12) with the prefilled diluent syringe provided. Do not detach the prefilled diluent syringe until you are ready to attach the larger luer lock syringe to the next vial. Keep the vial adapter attached to the vial as you will need it for attaching a larger luer lock syringe. Use a larger luer lock plastic syringe to combine the contents of the reconstituted vials into the syringe, similar as described in Steps 13–14. Repeat this pooling procedure with each vial you will be using. Once you have pooled the required dose, proceed with the administration steps using the larger luer lock syringe.
13. Make sure the plunger rod is pressed all the way down and the diluent syringe is firmly attached to the vial adapter. Turn the vial upside-down. Slowly pull down on the plunger rod to draw all the solution from the vial into the diluent syringe. Be careful not to pull the plunger rod completely out of the diluent syringe.
14. Gently unscrew the diluent syringe from the vial adapter by turning it to the right. Dispose of the vial with the adapter still attached. If you are not ready to inject, put the syringe cap carefully back onto the syringe tip. Do not touch the syringe tip or the inside of the cap.
15. Use the reconstituted ALTUVIIIO as soon as possible, but no later than 3 hours after reconstitution. Do not touch the glass tip of the syringe if not used immediately after reconstitution. Protect from direct sunlight. Do not refrigerate after reconstitution.

2.3 Administration

For intravenous use only.

- Parenteral drug products should be inspected visually for particulate matter and discoloration prior to administration, whenever solution and container permit. Do not use ALTUVIIIO solution if particulate matter or discoloration is observed.
- Do not administer reconstituted ALTUVIIIO in the same tubing or container with other medications.

Administration Steps:

1. Attach the syringe to the connector end of the infusion set tubing by turning it to the right until it is securely attached.
2. Push the plunger rod until all air is removed from the syringe and ALTUVIIIO has filled the infusion set needle. Do not push ALTUVIIIO solution through the needle.
3. Remove the protective needle cover from the infusion set needle.
4. Perform intravenous injection slowly over 1 to 10 minutes, based on the patient's comfort level.
5. After infusing ALTUVIIIO, remove and properly discard the infusion set.

3 DOSAGE FORMS AND STRENGTHS

ALTUVIIIO is available as a white to off-white lyophilized powder for reconstitution in single-dose vials containing nominally 250, 500, 750, 1000, 2000, 3000, or 4000 international units (IU) per vial.

4 CONTRAINDICATIONS

ALTUVIIIO is contraindicated in patients who have had severe hypersensitivity reactions, including anaphylaxis, to the product or its excipients [see Description (11)].

5 WARNINGS AND PRECAUTIONS

5.1 Hypersensitivity Reactions

Hypersensitivity reactions, including anaphylaxis, have occurred with ALTUVIIIO [see Postmarketing Experience (6.2)]. Signs and symptoms include, but not limited to, hives, shortness of breath, chest tightness, wheezing, hypotension, nausea, vomiting, and itching. Discontinue ALTUVIIIO if hypersensitivity reaction occurs and manage symptoms as appropriate.

5.2 Neutralizing Antibodies

Formation of neutralizing antibodies (inhibitors) to Factor VIII has been reported following administration of ALTUVIIIO [see Postmarketing Experience (6.2)]. Monitor all patients for the development of Factor VIII inhibitors by appropriate clinical observations and laboratory tests. If the patient's plasma Factor VIII level fails to increase as expected or if bleeding is not controlled after ALTUVIIIO administration, the presence of an inhibitor (neutralizing antibodies) should be suspected, and appropriate testing performed [see Warnings and Precautions (5.3)].

5.3 Monitoring Laboratory Tests

If assessment of plasma Factor VIII activity is needed, it is recommended to use a validated one-stage clotting assay [see Dosage and Administration (2)]. The ALTUVIIIO Factor VIII activity level is overestimated by the chromogenic assay and a specific ellagic acid based aPTT reagent in one-stage clotting assay by approximately 2.5-fold. If these assays are used, divide the result by 2.5 to approximate the patient's ALTUVIIIO Factor VIII activity level. Use of a reference laboratory is recommended when a qualified one-stage clotting assay or chromogenic assay is not available locally.

Monitor for the development of Factor VIII inhibitors. If bleeding is not controlled with ALTUVIIIO and the expected factor VIII activity plasma levels are not attained, perform an assay to determine if Factor VIII inhibitors are present (use Bethesda Units to titer inhibitors).

6 ADVERSE REACTIONS

6.1 Clinical Trials Experience

Because clinical trials are conducted under widely varying conditions, adverse reaction rates observed in the clinical trials of a drug cannot be directly compared to rates in the clinical trials of another drug and may not reflect the rates observed in practice.

The safety data described in this section reflects exposure to ALTUVIIIO in two clinical studies, Study 1 and Study 2 and are pooled for analysis. In Study 1, a total of 159 previously treated patients (PTPs) (134 adults and 25 adolescents) with severe Hemophilia A) received at least one dose of ALTUVIIIO for either routine prophylaxis, on-demand treatment of bleeding episodes or perioperative management. A total of 152 (96%) patients achieved at least 25 exposure days and 115 (72%) patients achieved at least 50 exposure days with a median of 53.0 (range 2–63) for both exposure days and injections per patient. Overall exposure was monitored for a total of 151.5 patient-years [see Clinical Studies (14)].

In Study 2, the safety of ALTUVIIIO was evaluated in 74 male PTPs <12 years of age with severe hemophilia A who received at least one dose of ALTUVIIIO. Sixty-six (89.2%) patients achieved at least 50 exposure days with a median of 53.0 (range 3–72).

Adverse events were monitored for a total of 210.7 patient-years in 2 completed clinical studies in PTPs. Adverse drug reactions (ADRs) (summarized in Table 3) were reported in 79 (33.9%) of the 233 patients treated with routine prophylaxis or on-demand therapy. The most common ADRs (>10%) in adults and adolescents were headache (20.1%) and arthralgia (16.4%). In children below 12 years, pyrexia (12.2%) was the most common ADR (>10%). In the studies, no inhibitors to FVIII were detected and no ADRs of anaphylaxis were reported.

The most common adverse reactions (>10% of patients) reported in clinical trials were headache and arthralgia.

Table 3: Adverse Reactions with Frequency of ≥3% Reported in ALTUVIIIO Studies [Pooled data from Study 1 and Study 2 including 233 patients across the adult and adolescent and pediatric studies.]
MedDRA System Organ Class | Adverse Drug Reactions | Number of Patients n (%) (N = 233)
Nervous system disorders | Headache | 35 (15)
Musculoskeletal and connective tissue disorders | Arthralgia | 31 (13)
Musculoskeletal and connective tissue disorders | Pain in extremity | 10 (4)
Musculoskeletal and connective tissue disorders | Back pain | 9 (4)
General disorders and administration | Pyrexia | 10 (4)
Gastrointestinal disorders | Vomiting | 7 (3)

Thromboembolic events occurred in 1% (3/261) of patients in the long-term safety extension study; these three patients had pre-existing risk factors.

6.2 Postmarketing Experience

The following adverse reactions have been identified during the post approval use of ALTUVIIIO. Because these reactions are reported voluntarily from a population of uncertain size, it is not always possible to reliably estimate their frequency or establish a causal relationship to drug exposure.

Blood and lymphatic system disorders: Factor VIII inhibitor development [see Warnings and Precautions (5.2)].

Immune system disorders: Hypersensitivity reactions, including anaphylaxis [see Warnings and Precautions (5.1)].

8 USE IN SPECIFIC POPULATIONS

8.1 Pregnancy

Risk Summary

There are no data with ALTUVIIIO use in pregnant women to inform a drug-associated risk. Animal developmental and reproductive studies have not been conducted with ALTUVIIIO. Therefore, it is not known whether ALTUVIIIO can affect reproductive capacity or cause fetal harm when given to pregnant women.

In the U.S. general population, the estimated background risk of major birth defects and miscarriage in clinically recognized pregnancies is 2–4% and 15–20%, respectively.

8.2 Lactation

Risk Summary

There is no information regarding the presence of ALTUVIIIO in human milk, its effects on the breastfed infant, or its effects on milk production. The developmental and health benefits of breastfeeding should be considered along with the mother's clinical need for ALTUVIIIO and any potential adverse effects on the breastfed infant from ALTUVIIIO or from the underlying maternal condition.

8.4 Pediatric Use

The safety and effectiveness of ALTUVIIIO for routine prophylaxis, on-demand treatment, and perioperative management of bleeding episodes have been established in pediatric patients <18 years old. The use of ALTUVIIIO for these indications is supported by evidence from two clinical studies which enrolled 99 previously treated patients <18 years of age who received at least one dose of ALTUVIIIO as part of routine prophylaxis, treatment of bleeding episodes, or perioperative management. Thirty-eight patients (38.4%) were <6 years of age, 36 (36.4%) patients were 6 to <12 years of age, and 25 patients (25.2%) were adolescents (12 to <18 years of age). Data from the pediatric study (74 patients) <12 years of age showed that no dosing adjustment was required [see Adverse Reactions (6.1), Clinical Pharmacology (12), and Clinical Studies (14)].

8.5 Geriatric Use

Clinical studies of ALTUVIIIO did not include sufficient numbers of patients 65 years of age and older to determine whether or not such patients respond differently from younger patients. However, clinical experience with other Factor VIII products has not identified differences between the elderly and younger patients.

11 DESCRIPTION

ALTUVIIIO [antihemophilic factor (recombinant), Fc-VWF-XTEN fusion protein-ehtl] is a sterile, non-pyrogenic, white to off-white lyophilized powder for reconstitution for intravenous injection. The product is supplied in single-dose vials containing nominal potencies of 250, 500, 750, 1000, 2000, 3000, or 4000 international units (IU). Each vial of ALTUVIIIO is labeled with the actual Factor VIII activity content in IU. The powder for injection is reconstituted with 3 mL sterile water for injection (sWFI) supplied in a sterile prefilled syringe. The reconstituted solution should be essentially free of particles. The final product contains the excipients: arginine hydrochloride (250 mM), calcium chloride dihydrate (5 mM), histidine (10 mM), polysorbate 80 (0.05% w/v), and sucrose (5% w/v).

The active ingredient in ALTUVIIIO is a fully recombinant fusion protein comprising a single chain B-domain deleted (BDD) analogue of human FVIII covalently fused to the Fc domain of human immunoglobulin G1 (IgG1), the FVIII-binding D'D3 domain of human von Willebrand factor (VWF), and 2 XTEN polypeptides. ALTUVIIIO contains 2829 amino acids with an apparent molecular weight of 312 kDa. ALTUVIIIO is synthesized as 2 polypeptide chains which are covalently linked by 2 Fc hinge disulfide bonds. The first FVIII-XTEN-Fc polypeptide chain contains the A1A2 domain of FVIII along with 5 amino acids from B-domain (1–745 amino acids) fused to the 288-XTEN polypeptide (in place of the natural FVIII B-domain), the A3C1C2 domain of FVIII (1649–2332), and the Fc domain of human IgG1. The second VWF-XTEN-a2-Fc polypeptide chain contains the D'D3 domain of VWF (1–477 amino acids) fused to the 144-XTEN polypeptide, a thrombin cleavable acidic region 2 sequence from FVIII and the Fc domain of human IgG1. The Fc domain includes the hinge, CH2, and CH3 domains of IgG1. The Fc, VWF, and XTEN polypeptide portions of the molecule extend the half-life of ALTUVIIIO in plasma.

ALTUVIIIO is produced by recombinant DNA technology in a human embryonic kidney (HEK) cell line, which has been extensively characterized. ALTUVIIIO is manufactured without addition of human- or animal-derived components and purified by a combination of multiple chromatography steps, a detergent or solvent/detergent viral inactivation step, a nano filtration step for viral clearance, and ultrafiltration steps.

12 CLINICAL PHARMACOLOGY

12.1 Mechanism of Action

ALTUVIIIO temporarily replaces the missing coagulation factor VIII needed for effective hemostasis. ALTUVIIIO has demonstrated 3- to 4-fold prolonged half-life relative to other standard and extended half-life FVIII products.

Mechanism of Half-life Extension

ALTUVIIIO is a recombinant FVIII analogue fusion protein that is independent of endogenous VWF in order to overcome the half-life limit imposed by FVIII-VWF interactions. The D'D3 domain of VWF is the region that interacts with FVIII. Appending the D'D3 domain of VWF to a recombinant FVIII-Fc fusion protein provides protection and stability to FVIII, and prevents FVIII interaction with endogenous VWF, thus overcoming the limitation on FVIII half-life imposed by VWF clearance.

The Fc region of human immunoglobulin G1 (IgG1) binds to the neonatal Fc receptor (FcRn). FcRn is part of a naturally occurring pathway that delays lysosomal degradation of immunoglobulins by recycling them back into circulation, thus prolonging the plasma half-life of the fusion protein.

ALTUVIIIO contains 2 XTEN polypeptides, which alter the hydrodynamic radius of the fusion protein, thus reducing rates of clearance and degradation, and improving pharmacokinetic properties. In ALTUVIIIO, the natural FVIII B domain (except 5 amino acids) is replaced with the first XTEN polypeptide, inserted in between FVIII N745 and E1649 amino acid residues; and the second XTEN polypeptide is inserted in between the D'D3 domain and Fc.

12.2 Pharmacodynamics

Hemophilia A is a bleeding disorder characterized by a deficiency of functional coagulation factor VIII (FVIII), which leads to a prolonged clotting time in the activated partial thromboplastin time (aPTT)-based one-stage clotting assay. Administration of ALTUVIIIO increases plasma levels of FVIII, temporarily correcting the coagulation defect in hemophilia A patients.

Based on FVIII pharmacokinetic/pharmacodynamic analyses, the risk of bleeding is negatively correlated with FVIII activity. Once weekly 50 IU/kg ALTUVIIIO provided factor VIII activity levels that were associated with a low bleed risk.

12.3 Pharmacokinetics

The PK of ALTUVIIIO were evaluated in prospective, open-label clinical studies, enrolling 159 adults and adolescents, and 74 children <12 years old, respectively, receiving weekly IV injections of 50 IU/kg. Among children <12 years old, 37 patients had ALTUVIIIO single dose PK profiles available.

PK parameters following a single dose of ALTUVIIIO are presented in Table 4. The PK parameters were based on plasma FVIII activity measured by the aPTT-based one-stage clotting assay. After a single dose of 50 IU/kg, ALTUVIIIO exhibited high sustained FVIII activity with prolonged half-life across age cohorts. There was a trend of increasing area under the curve (AUC), and decreasing clearance, with increasing age in the pediatric cohorts. The PK profile at steady state (Week 26) was comparable with the PK profile obtained after the first dose.

Table 4: Pharmacokinetic Parameters Following a Single Dose of ALTUVIIIO by age (one-stage clotting assay)
PK Parameters (mean SD) | Pediatric Study | Pediatric Study | Adult and Adolescent Study | Adult and Adolescent Study
 | 1 to <6 Years N = 18 | 6 to <12 Years N = 18 | 12 to <18 years N = 25 | Adults N = 134
AUC (IU×h/dL) | 6800 (1120) [N = 17] | 7190 (1450) | 8350 (1550) | 9850 (2010) [Calculation based on 128 profiles.]
t1/2 (h) | 38.0 (3.7) | 42.4 (3.7) | 44.6 (5.0) | 48.2 (9.3)
CL (mL/h/kg) | 0.742 (0.121) | 0.681 (0.139) | 0.582 (0.115) | 0.493 (0.121)
Vss (mL/kg) | 36.6 (5.6) | 38.1 (6.8) | 34.9 (7.4) | 31.0 (7.3)
MRT (hr) | 49.6 (5.5) | 56.3 (5.1) | 60.0 (5.5) | 63.9 (10.2)
AUC0–tau = area under the activity-time curve over the dosing interval, CL = clearance, MRT = mean residence time, SD = standard deviation, t1/2z = terminal half-life, Vss = volume of distribution at steady state.

ALTUVIIIO at steady state maintained normal to near normal (>40 IU/dL) FVIII activity for a mean (SD) of 4.1 (0.7) days with once weekly prophylaxis in adults. The FVIII activity over 10 IU/dL was maintained in 83.5% of adults and adolescent patients throughout the study. In children <12 years ALTUVIIIO maintained normal to near normal (>40 IU/dL) FVIII activity for 2 to 3 days and >10 IU/dL FVIII activity for approximately 7 days (see Table 5).

Table 5: Pharmacokinetic Parameters at Steady State of ALTUVIIIO by age (one-stage clotting assay)
PK Parameters Mean (SD) | Pediatric Study [Steady state peak, trough and IR were computed using available measurements at week 52/End of study PK sampling visit.] | Pediatric Study | Adult and Adolescent Study | Adult and Adolescent Study
 | 1 to <6 years N = 37 | 6 to <12 years N = 36 | 12 to <18 years N = 24 | Adults N = 125
Peak (IU/dL) | 136 (49) (N = 35) | 131 (36) (N = 35) | 124 (31) | 150 (35) (N = 124)
IR (kg×IU/dL/IU) | 2.22 (0.83) (N = 35) | 2.10 (0.73) (N = 35) | 2.25 (0.61) (N = 22) | 2.64 (0.61) (N = 120)
Time to 40 IU/dL (h) | 68.0 (10.5) [Time to FVIII activity was predicted using population PK model for pediatric study.] | 80.6 (12.3) | 81.5 (12.1) [Time to FVIII activity was predicted using population PK model for adult study.] | 98.1 (20.1)
Time to 20 IU/dL (h) | 109 (14) | 127 (15) | 130 (16) | 150 (28)
Time to 10 IU/dL (h) | 150 (18) | 173 (17) | 179 (20) | 201 (36)
Trough (IU/dL) | 10.9 (19.7) (N = 36) | 16.5 (23.7) | 9.23 (4.77) (N = 22) | 18.0 (16.6) (N = 123)
Peak = 15 min post dose at steady state, IR = incremental recovery, Trough – predose FVIII activity value at steady state, SD = standard deviation.

Specific Populations

The following factors have no clinically meaningful effect on the pharmacokinetics of ALTUVIIIO: age (1.4 to 72 years), sex, race (White, Asian), VWF activity (40 to 339 IU/dL), hematocrit level (28% to 57%), blood type, HCV status, or HIV status. Body weight (12.5 to 133 kg) is expected to alter weight normalized clearance (dL/h/kg) by 79% to -18% compared to a typical patient.

12.6 Immunogenicity

The observed incidence of anti-drug antibodies (ADAs) is highly dependent on the sensitivity and specificity of the assay. Differences in assay methods preclude meaningful comparisons of the incidence of anti-drug antibodies in the studies described below with the incidence of anti-drug antibodies in other studies, or of other Factor VIII products.

In Study 1 and Study 2, all patients were monitored for neutralizing antibodies (inhibitors) to Factor VIII in the clinical program. No patients developed neutralizing antibodies to Factor VIII. Factor VIII inhibitor development has occurred in the postmarketing setting [see Postmarketing Experience (6.2)].

During ALTUVIIIO clinical studies (median treatment duration 96.3 weeks), 4/276 (1.4%) of evaluable patients developed transient treatment emergent anti-drug antibodies.

No impact of ADAs on the FVIII activity levels or PK exposure parameters was observed.

No impact of ADAs with respect to bleeding episodes pharmacodynamic response, or safety was noted.

13 NONCLINICAL TOXICOLOGY

13.1 Carcinogenesis, Mutagenesis, Impairment of Fertility

No carcinogenicity or mutagenicity studies have been conducted with of ALTUVIIIO. No studies have been conducted to evaluate the effects of ALTUVIIIO on fertility.

14 CLINICAL STUDIES

The safety, efficacy, and pharmacokinetics of ALTUVIIIO were evaluated in two multicenter, prospective, open-label clinical studies, Study 1 (NCT04161495) and Study 2 (NCT04759193), as described below.

All studies evaluated the efficacy of routine prophylaxis with a weekly dose of 50 IU/kg and determined hemostatic efficacy in the treatment of bleeding episodes and during perioperative management in patients undergoing major or minor surgical procedures.

Routine Prophylaxis to Reduce Bleeding Episodes

Study 1 (Adult and Adolescent Study)

Study 1 enrolled a total of 159 previously treated patients (PTPs) including 158 male and 1 female patients with severe hemophilia A (<1% endogenous Factor VIII activity or a documented genetic mutation). Patients were aged 12 to 72 years and included 25 adolescent patients aged 12 to 17 years. All 159 enrolled patients received at least one dose of ALTUVIIIO and were evaluable for efficacy. A total of 149 patients (93.7%) completed the study.

The efficacy of weekly 50 IU/kg ALTUVIIIO as routine prophylaxis was evaluated as estimated by the mean annualized bleed rate (ABR) and by comparing the ABR during on-study prophylaxis vs. the ABR during pre-study FVIII prophylaxis. A total of 133 adults and adolescents, who were on pre-study FVIII prophylaxis, were assigned to receive ALTUVIIIO for routine prophylaxis at a dose of 50 IU/kg IV once weekly for 52 weeks (Arm A). An additional 26 patients, who were on pre-study episodic (on-demand) treatment with FVIII, received episodic (on-demand) treatment with ALTUVIIIO at doses of 50 IU/kg IV for 26 weeks, followed by routine prophylaxis at a dose of 50 IU/kg IV once weekly for 26 weeks (Arm B). Overall, 115 patients received at least a total number of 50 exposure days (EDs) in Arm A and 17 patients completed at least 25 EDs of routine prophylaxis in Arm B.

The ABR in patients evaluable for efficacy with at least 26 weeks of exposure are summarized in Table 6.

Table 6: Summary of Annualized Bleeding Rate (ABR) with ALTUVIIIO Prophylaxis, ALTUVIIIO On-demand Treatment, and After Switch to ALTUVIIIO Prophylaxis in Patients ≥12 Years of Age (Study 1)
Endpoint [Reflects all bleeds reported by patients including those where no ALTUVIIIO was administered.] | Arm A Prophylaxis [Patients assigned to receive ALTUVIIIO prophylaxis for 52 weeks.] | Arm B On-demand [Patients assigned to receive ALTUVIIIO for 26 weeks.] | Arm B Prophylaxis
 | N = 128 | N = 26 | N = 26
Treated bleeds
Mean ABR (95% CI) [Based on negative binomial model.] | 0.7 (0.5, 1.0) | 21.4 (18.8, 24.4) | 0.7 (0.3, 1.5)
Median ABR (Q1, Q3) | 0 (0, 1.0) | 21.1 (15.1, 27.1) | 0 (0, 0)
% patients with zero bleeds, n (%) | 82 (64.1) | 0 | 20 (76.9)
Treated spontaneous bleeds
Mean ABR (95% CI) | 0.3 (0.2, 0.4) | 15.8 (12.3, 20.4) | 0.4 (0.2, 1.2)
Median ABR (Q1, Q3) | 0 (0, 0) | 16.7 (8.6, 23.8) | 0 (0, 0)
% patients with zero bleeds, n (%) | 103 (80.5) | 1 (3.8) | 22 (84.6)
Treated joint bleeds
Mean ABR (95% CI) | 0.5 (0.4, 0.7) | 17.5 (14.9, 20.5) | 0.6 (0.3, 1.5)
Median ABR (Q1, Q3) | 0 (0, 1.0) | 18.4 (10.8, 23.9) | 0 (0, 0)
% patients with zero bleeds, n (%) | 92 (71.9) | 0 | 21 (80.8)
All Bleeds (treated and untreated)
Mean ABR (95% CI) | 1.1 (0.8, 1.5) | 22.2 (19.4, 25.4) | 0.9 (0.4, 1.8)
Median ABR (Q1, Q3) | 0 (0, 1.2) | 21.1 (16.8, 27.1) | 0 (0, 1.9)
% patients with zero bleeds, n (%) | 71 (55.5) | 0 | 19 (73.1)
ABR = annualized bleed rate; CI = confidence interval; Q1 = 25th percentile, Q3 = 75th percentile.

An intra-patient comparison (N = 78) between mean ABR during on-study prophylaxis with ALTUVIIIO and that during pre-study FVIII prophylaxis yielded a 77% reduction in treated bleeds (95% CI: 58%, 87%).

All patients with target joints at baseline (defined as ≥3 spontaneous bleeding episodes in a major joint which occurred in a consecutive 6-month period) achieved resolution of all target joints (45/45, 100%) with 12 months of prophylactic treatment with ALTUVIIIO (defined as ≤2 bleeding episodes in the target joint in 12 months).

Study 2 (Pediatric Study)

Study 2 enrolled 74 male PTPs <12 years of age with severe hemophilia A (38 patients were 1 to 5 years of age and 36 were 6 to 11 years of age). Of the 74 enrolled patients, all received at least 1 dose of ALTUVIIIO. Seventy-two patients were evaluable for efficacy.

The efficacy of weekly 50 IU/kg ALTUVIIIO as routine prophylaxis in children <12 years was evaluated as estimated by the mean annualized bleed rate (ABR). A total of 74 children (38 children <6 years of age and 36 children 6 to <12 years of age) were enrolled to receive ALTUVIIIO for routine prophylaxis at a dose of 50 IU/kg IV once weekly for 52 weeks.

The ABR in patients evaluable for efficacy with at least 26 weeks of exposure are summarized in Table 7.

Table 7: Summary of Annualized Bleeding Rate (ABR) with ALTUVIIIO Prophylaxis in Patients <12 Years of Age (Study 2)
Endpoint [Reflects all bleeds reported by patients including those where no ALTUVIIIO was administered.] | <6 years | 6 to <12 years | Overall
 | N = 37 [A patient in the <6 years old age group who had a positive inhibitor result at baseline (pre-exposure to study drug) and was withdrawn after 3 EDs was excluded.] | N = 35 [A patient in the 6 to <12 years old age group who received an intense consolidation treatment (2 to 3 injections per week) for 15 weeks, after 2 traumatic hip joint bleeds was excluded from the efficacy analysis as the patient did not receive the weekly prophylaxis treatment as specified in the protocol for an extended period.] | N = 72
Treated bleeds
Mean ABR (95% CI) [Based on negative binomial model.] | 0.5 (0.3, 0.8) | 0.8 (0.4, 1.4) | 0.6 (0.4, 0.9)
Median ABR (Q1, Q3) | 0 (0, 1.0) | 0 (0, 1.1) | 0 (0, 1.0)
% patients with zero bleeds, n (%) | 23 (62.2) | 23 (65.7) | 46 (63.9)
Treated spontaneous bleeds
Mean ABR (95% CI) | 0.2 (0.1, 0.4) | 0.2 (0, 0.6) | 0.2 (0.1, 0.3)
Median ABR (Q1, Q3) | 0 (0, 0) | 0 (0, 0) | 0 (0, 0)
% patients with zero bleeds, n (%) | 31 (83.8) | 32 (91.4) | 63 (87.5)
Treated joint bleeds
Mean ABR (95% CI) | 0.2 (0.1, 0.6) | 0.4 (0.2, 0.9) | 0.3 (0.2, 0.6)
Median ABR (Q1, Q3) | 0 (0, 0) | 0 (0, 0) | 0 (0, 0)
% patients with zero bleeds, n (%) | 33 (89.2) | 27 (77.1) | 60 (83.3)
All Bleeds (treated and untreated)
Mean ABR (95% CI) | 2.8 (1.4, 5.6) | 2.3 (1.3, 4.1) | 2.6 (1.6, 4.0)
Median ABR (Q1, Q3) | 0 (0, 2.0) | 1.0 (0, 2.9) | 0.5 (0, 2.1)
% patients with zero bleeds, n (%) | 20 (54.1) | 16 (45.7) | 36 (50.0)
ABR = annualized bleed rate; CI = confidence interval; Q1 = 25th percentile, Q3 = 75th percentile.

Efficacy in Control of Bleeding

In the adult and adolescent study, a total of 362 bleeding episodes were treated with ALTUVIIIO, most occurring during on-demand treatment in Arm B. Majority of bleeding episodes were localized in joints. Response to the first injection was assessed by patients at least 8 hours after treatment. A 4-point rating scale of excellent, good, moderate, and no response was used to assess response. Bleeding was resolved with a single 50 IU/kg injection of ALTUVIIIO in 96.7% of bleeding episodes. The median (Q1; Q3) total dose to treat a bleeding episode was 50.9 IU/kg (50.0; 51.9). Control of bleeding episodes was similar across the treatment arms.

The efficacy of ALTUVIIIO in control of bleeding in children <12 years of age was assessed in the pediatric study. A total of 43 bleeding episodes were treated with ALTUVIIIO. Bleeding was resolved with a single 50 IU/kg injection of ALTUVIIIO in 95.3% of bleeding episodes. The median (Q1; Q3) total dose to treat a bleeding episode was 52.6 IU/kg (50.0; 55.8).

Perioperative Management of Bleeding

Perioperative hemostasis was assessed in 14 major surgeries in 13 patients (10 adults and 3 children) across the adult and adolescent and pediatric clinical studies. Of the 14 major surgeries, 13 surgeries required a single pre-operative dose to maintain hemostasis during surgery; for 1 major surgery during routine prophylaxis no pre-operative loading dose was administered on the day of/or before surgery. The median pre-operative dose per surgery was 50 IU/kg (range 12.7 – 61.9).

The clinical evaluation of hemostatic response during major surgery was assessed using a 4-point scale of excellent, good, moderate, or poor/none. The hemostatic effect of ALTUVIIIO was rated as "excellent" in 14 of 14 surgeries (100%).

Types of major surgeries assessed include major orthopedic procedures such as arthroplasties (joint replacements of knee, hip, and elbow), joint revisions and ankle fusion. Other major surgeries included molar tooth extractions, dental restoration and tooth extraction, circumcision, and rhinoplasty/mentoplasty.

Perioperative hemostasis was assessed in 27 minor surgeries in 23 patients (12 adults and 11 adolescents and children). The hemostatic response was evaluated by the investigator/surgeon in 21 of these minor surgeries; an excellent response was reported in all (100%).

16 HOW SUPPLIED/STORAGE AND HANDLING

How Supplied

ALTUVIIIO is supplied in kits comprising a single-dose vial containing nominally, 250, 500, 750, 1000, 2000, 3000, or 4000 international units (IU) of Factor VIII potency, a prefilled syringe with 3 mL sterile water for injection, and a sterile vial adapter (reconstitution device). The actual amount of ALTUVIIIO in IU is stated on the label and carton of each vial.

Not made with natural rubber latex.

Strength | Potency Color Code | Kit NDC Number
250 IU | Yellow | 71104-978-01
500 IU | Red | 71104-979-01
750 IU | Garnet | 71104-980-01
1000 IU | Green | 71104-981-01
2000 IU | Royal Blue | 71104-982-01
3000 IU | Mist Grey | 71104-983-01
4000 IU | Orange | 71104-984-01

Not all pack sizes may be marketed.

Storage and Handling

Prior to reconstitution:

- Store ALTUVIIIO in the original package to protect the ALTUVIIIO vials from light.
- Store ALTUVIIIO in powder form at 2°C to 8°C (36°F to 46°F). Do not freeze to avoid damage to the prefilled diluent syringe.
- ALTUVIIIO may be stored at room temperature, not to exceed 30°C (86°F), for a single period of up to 6 months, within the expiration date printed on the label.
- If stored at room temperature, record the date that ALTUVIIIO is removed from refrigeration on the carton in the area provided. After storage at room temperature, do not return the product to the refrigerator.
- Do not use beyond the expiration date printed on the vial or 6 months after the date that was written on the carton, whichever is earlier.

After Reconstitution:

- The reconstituted product may be stored at room temperature, not to exceed 30°C (86°F), for up to 3 hours. Protect from direct sunlight. After reconstitution, if the product is not used within 3 hours, it must be discarded.
- Do not use ALTUVIIIO if the reconstituted solution is cloudy or has particulate matter.
- Discard any unused ALTUVIIIO.

17 PATIENT COUNSELING INFORMATION

Advise the patients to:

- Read the FDA-approved patient labeling (Patient Information and Instructions for Use).
- Call their healthcare provider or go to the emergency department right away if a hypersensitivity reaction occurs. Early signs of hypersensitivity reactions may include rash, hives, itching, facial swelling, tightness of the chest, and wheezing.
- Contact their healthcare provider or treatment facility for further treatment and/or assessment if they experience a lack of a clinical response to Factor VIII therapy because this may be a sign of inhibitor development.

Manufactured by:
Bioverativ Therapeutics Inc.
Waltham, MA 02451
A SANOFI COMPANY
US License Number 2078

©2025 Bioverativ Therapeutics Inc. All rights reserved.

For patent information: https://www.sanofi.us/en/products-and-resources/patents

ALTUVIIIO is a registered trademark of Bioverativ Therapeutics Inc.

Patient Information

ALTUVIIIO® (al too'vee oh)

[antihemophilic factor (recombinant), Fc-VWF-XTEN fusion protein-ehtl]

for intravenous use after reconstitution only

Single-dose vial

Please read this Patient Information carefully before using ALTUVIIIO and each time you get a refill, as there may be new information. This Patient Information does not take the place of talking with your healthcare provider about your medical condition or your treatment.

What is the most important information I need to know about ALTUVIIIO?

Do not attempt to give yourself an injection unless you have been taught how by your healthcare provider or hemophilia center.

You must carefully follow your healthcare provider's instructions regarding the dose and schedule for injecting ALTUVIIIO so that your treatment will work best for you.

What is ALTUVIIIO?

ALTUVIIIO is an injectable medicine that is used to control and reduce the number of bleeding episodes in people with Hemophilia A (congenital Factor VIII deficiency).

Your healthcare provider may give you ALTUVIIIO when you have surgery.

Who should not use ALTUVIIIO?

You should not use ALTUVIIIO if you had an allergic reaction to it in the past.

What should I tell my healthcare provider before using ALTUVIIIO?

Talk to your healthcare provider about:

- Any medical problems that you have or had.
- All prescription and non-prescription medicines that you take, including over-the-counter medicines, supplements or herbal medicines.
- Pregnancy or if you are planning to become pregnant. It is not known if ALTUVIIIO may harm your unborn baby.
- Breastfeeding. It is not known if ALTUVIIIO passes into the milk and if it can harm your baby.

How should I use ALTUVIIIO?

You get ALTUVIIIO as an injection into your vein. Your healthcare provider will instruct you on how to do injections on your own and may watch you give yourself the first dose of ALTUVIIIO.

Contact your healthcare provider right away if bleeding is not controlled after using ALTUVIIIO.

What are the possible side effects of ALTUVIIIO?

You can have an allergic reaction to ALTUVIIIO. Call your healthcare provider or emergency department right away if you have any of the following symptoms: difficulty breathing, chest tightness, swelling of the face, rash or hives.

Your body can also make antibodies called "inhibitors" against ALTUVIIIO. This can stop ALTUVIIIO from working properly. Your healthcare provider may give you blood tests to check for inhibitors.

The common side effects of ALTUVIIIO are headache and joint pain.

These are not the only possible side effects of ALTUVIIIO. Tell your healthcare provider about any side effect that bothers you or does not go away.

What are the ALTUVIIIO dosage strengths?

ALTUVIIIO comes in seven different dosage strengths with 3 mL sterile water for injection (sWFI). The actual number of international units (IU) of Factor VIII activity in the vial will be imprinted on the label and on the box. The seven different strengths are as follows:

Strength | Cap Color
250 IU | Yellow
500 IU | Red
750 IU | Garnet
1000 IU | Green
2000 IU | Royal Blue
3000 IU | Mist Grey
4000 IU | Orange

Always check the actual dosage strength printed on the label to make sure you are using the strength prescribed by your healthcare provider.

How should I store ALTUVIIIO?

- Keep ALTUVIIIO in its original package.
- Protect it from light.
- Do not freeze.
- Store refrigerated 2°C to 8°C (36°F to 46°F) up to 48 months or at room temperature [not to exceed 30°C (86°F)], for a single period up to 6 months. Do not use ALTUVIIIO after the expiration date printed on the label and carton of each vial.
- When storing at room temperature:
  - Note on the carton the date on which the product is removed from refrigeration.
  - Use the product before the end of this 6-month period or discard it.
  - Do not return the product to the refrigerator.

After mixing with the diluent:

- Do not use ALTUVIIIO if the mixed solution is not clear and colorless to slightly yellowish.
- Use mixed product as soon as possible.
- You may store mixed ALTUVIIIO at room temperature, not to exceed 30°C (86°F), for up to 3 hours. Protect the mixed ALTUVIIIO from direct sunlight. Discard any mixed ALTUVIIIO not used within 3 hours.

What else should I know about ALTUVIIIO?

Medicines are sometimes prescribed for purposes other than those listed here. Do not use ALTUVIIIO for a condition for which it was not prescribed. Do not share ALTUVIIIO with other people, even if they have the same symptoms that you have.

This Patient Information has been approved by the U.S. Food and Drug Administration.

Manufactured by:
Bioverativ Therapeutics Inc.
Waltham, MA 02451
A SANOFI COMPANY
US License Number 2078

©2024 Bioverativ Therapeutics Inc. All rights reserved.

ALTUVIIIO is a registered trademark of Bioverativ Therapeutics Inc.

Revised: SEP 2024

INSTRUCTIONS FOR USE
ALTUVIIIO® (al too'vee oh)
[antihemophilic factor (recombinant), Fc-VWF-XTEN fusion protein-ehtl]
for intravenous use after reconstitution only
Single-dose vial

Read the Instructions for Use before you start using ALTUVIIIO and each time you get a refill. There may be new information. This information does not take the place of talking to your healthcare provider about your medical condition or your treatment.

Your healthcare provider should show you or your caregiver how to mix (reconstitute) and give ALTUVIIIO the first time ALTUVIIIO is used.

Any further questions? Ask your healthcare provider or call 1-800-633-1610.

Important Information You Need to Know Before Injecting ALTUVIIIO

It is important that you do not try to inject ALTUVIIIO unless you have received training from a healthcare provider.

- Read all of the instructions carefully before using the ALTUVIIIO.
- ALTUVIIIO is supplied as a single-dose vial of powder for mixing (reconstitution). Before you inject ALTUVIIIO, you must mix (reconstitute) ALTUVIIIO powder with liquid (diluent) that comes in a prefilled diluent syringe.
- After the powder and diluent are mixed the medicine is given in the vein (intravenous injection).
- The vial and the diluent syringe are not made with natural rubber latex.
- Do not use ALTUVIIIO if it has been dropped on a hard surface or damaged.
- Do not use if the syringe cap has been removed or is not securely attached.
- Do not use the mixed ALTUVIIIO if it contains visible particles or is cloudy.
- Do not give mixed ALTUVIIIO in the same tubing or container with other medicines.

Storing ALTUVIIIO

- Keep unused ALTUVIIIO kit in the original carton and store in the refrigerator between 2ºC and 8ºC (36ºF and 46ºF). The product may be stored at room temperature up to 30ºC (86ºF). If stored at room temperature, the product (prior to mixing) expires after 6 months or after the expiration date on the product vial, whichever is earlier.
- Remove the product kit from the refrigerator and allow the ALTUVIIIO vial and the prefilled diluent syringe to come to room temperature prior to injection.
- Do not use external heat sources such as putting the vial or prefilled diluent syringe in hot water.
- Do not return room temperature ALTUVIIIO to refrigerator.
- Keep away from direct sunlight.
- Do not freeze.

Storing of Mixed (Reconstituted) ALTUVIIIO

- ALTUVIIIO should be given within 3 hours after mixing.
- Keep away from direct sunlight.
- Do not refrigerate after mixing.
- Keep ALTUVIIIO and all medicines out of the reach of children.

Preparing to Inject ALTUVIIIO

Mixing (Reconstitution)

Step 1:

Look at the ALTUVIIIO kit:

- Check that you have the correct medicine and dose.
- Check the expiration date.

Do not use ALTUVIIIO if the expiration date has passed.

Step 2:

Wash your hands with soap and water.

Find a clean, flat work surface. Remove the supplies from the carton:

- Vial adapter in its package
- Vial with powdered medicine
- Plunger rod
- Prefilled diluent syringe

Also ensure you have the following supplies (not included in the carton):

- Infusion set
- Tourniquet
- 2 alcohol wipes
- 1 cotton ball or gauze pad
- 1 adhesive bandage, if required (See Step 22)
- 1 tape, if required (See Step 20)
- 1 larger luer lock syringe, if required (See Step 13)
- FDA-cleared sharps disposal container (See Step 23)

Do not use ALTUVIIIO (vial or prefilled diluent syringe) if it has been dropped on a hard surface or damaged.

Step 3:

Allow the ALTUVIIIO vial and the prefilled diluent syringe to come to room temperature before use.

Do not use external heat sources such as putting the vial or prefilled diluent syringe in hot water.

Do not put ALTUVIIIO in direct sunlight.

Do not return room temperature ALTUVIIIO to the refrigerator.

Step 4:

Remove the plastic cap from the ALTUVIIIO vial.

Wipe the rubber stopper of the vial with an alcohol wipe and allow it to dry.

After cleaning, do not touch the rubber stopper with your hand or allow it to touch any surface.

Step 5:

Completely remove the backing from the vial adapter package by peeling back the lid.

Do not remove the vial adapter from the package or touch the inside of the vial adapter.

Step 6:

Keep the vial on a flat surface. Hold the vial with one hand and using the other hand, place the vial adapter in its package over the vial.

Note: The spike should be placed directly above the center of the rubber stopper.

- Push the vial adapter straight down until the spike on the vial adapter punctures the center of the vial stopper and is fully inserted.

Step 7:

Lift the package cover away from the vial adapter and throw away the cover.

Step 8:

Note: Only use the prefilled diluent syringe provided to mix (reconstitute) the powdered medicine.

- Hold the plunger rod by the circular disk.
- Place the tip of the plunger rod into the end of the prefilled diluent syringe.
- Turn the plunger rod to the right until it is firmly attached.

Step 9:

With one hand, hold the prefilled diluent syringe directly under the cap with the cap pointing up.

Note: Make sure you are holding the prefilled diluent syringe by the ridged part directly under the cap.

Do not use if the cap has been removed or is not securely attached.

Step 10:

With your other hand, grasp the cap and bend it at a 90-degree angle until it snaps off.

Note: After the cap snaps off, you will see the glass tip of the prefilled diluent syringe.

Do not touch the glass tip of the prefilled diluent syringe or the inside of the cap.

Step 11:

Note: Be sure the vial is sitting on a flat surface.

- Insert the tip of the prefilled diluent syringe into the vial adapter opening.
- Turn the prefilled diluent syringe to the right until it is securely attached to the vial adapter.

Step 12:

Slowly push down on the plunger rod to inject all of the liquid (diluent) from the prefilled diluent syringe into the vial.

Note: The plunger rod may rise slightly afterward. This is normal.

Step 13:

With the prefilled diluent syringe still connected to the adapter, gently swirl the vial until the powder is completely dissolved.

Check the solution through the vial to make sure the powder is fully dissolved.

Note: The solution should look clear and colorless to slightly yellowish.

Do not shake.

Do not use the mixed (reconstituted) ALTUVIIIO if it contains visible particles or is cloudy.

POOLING: pooling is the process of combining two or more reconstituted vials into a larger luer lock syringe (not provided in the carton). If the dose requires more than one vial, reconstitute each vial as described above (See Steps 4–13) with the prefilled diluent syringe provided. Do not detach the prefilled diluent syringe until you are ready to attach the larger luer lock syringe to the next vial. Keep the vial adapter attached to the vial as you will need it for attaching a larger luer lock syringe. Use a larger luer lock plastic syringe to combine the contents of the reconstituted vials into the syringe, similar as described in Steps 14–15. Repeat this pooling procedure with each vial you will be using. Once you have pooled the required dose, proceed with Step 16 (Injecting ALTUVIIIO) using the larger luer lock syringe.

Step 14:

Make sure the plunger rod is pressed all the way down and the syringe is firmly attached to the vial adapter.

Turn the vial upside-down.

Slowly pull down on the plunger rod to draw all the solution from the vial into the syringe.

Note: Be careful not to pull the plunger rod completely out of the syringe.

Step 15:

Gently unscrew the syringe from the vial adapter by turning it to the right.

Throw away (dispose of) the vial with the adapter still attached (See Step 23).

If you are not ready to inject, put the syringe cap carefully back onto the syringe tip.

Do not touch the syringe tip or the inside of the cap.

Note: Mixed (reconstituted) ALTUVIIIO should be given within 3 hours after mixing.

Protect from direct sunlight. Do not refrigerate after reconstitution.

Injecting ALTUVIIIO

ALTUVIIIO is given in the vein (intravenous injection) after mixing (reconstitution) of the powdered medicine with the diluent.

These are very generic instructions so your healthcare provider should teach you how to inject ALTUVIIIO. After you have been taught to self-inject, you can follow these instructions.

Do not give mixed (reconstituted) ALTUVIIIO if it contains particles, is discolored, or is cloudy.

Step 16:

Using aseptic technique (clean and germ free), attach the syringe to the connector end of the infusion set tubing by turning it to the right until securely attached.

Do not give mixed (reconstituted) ALTUVIIIO in the same tubing or container with other medicines.

Note: Ask your healthcare provider which infusion set can be used with ALTUVIIIO.

Step 17:

Apply a tourniquet to the upper arm. Then, using a new alcohol wipe, clean the skin where you will insert the needle and wait for it to dry.

Step 18:

Prime the syringe and the tubing. Push the plunger rod until all air is removed from the syringe and ALTUVIIIO has filled the infusion set needle.

Do not push ALTUVIIIO through the needle.

Step 19:

Remove the protective needle cover from the infusion set needle and throw away (discard it).

Do not touch the needle and do not put the needle cover back onto needle after use.

- Insert the needle on the infusion set tubing into the vein as instructed by your healthcare provider.

Step 20:

Use tape to secure the plastic wings of the needle in place at the injection site if needed.

Remove the tourniquet.

Note: Always make sure you have correctly inserted the needle into a vein when you perform an intravenous injection.

Step 21:

Slowly push the plunger rod on the syringe all the way down to give ALTUVIIIO.

Your healthcare provider will provide your rate of administration based on your comfort level and the minimum injection time recommendation per vial.

Note: A small amount of medicine will be left in the infusion set after injection. This is normal.

Step 22:

After delivering ALTUVIIIO, remove the tape and the needle from the vein. Use a cotton ball or gauze pad to put pressure on the injection site for several minutes to stop any bleeding.

Note: You may apply an adhesive bandage if needed.

Step 23:

Put the infusion set and the syringe in FDA-cleared sharps disposal container right away after use.

Dispose of all unused solution according to your local regulations.

Dispose of all empty vial(s), and other used medical supplies in your household trash.

Do not throw away (dispose of) the infusion set or syringe in your household trash.

Disposing of ALTUVIIIO

Throw away (dispose of) the infusion set and the syringe in FDA-cleared sharps disposal container right away after use.

If you do not have FDA-cleared sharps disposal container you may use a household container that is:

- made of a heavy-duty plastic,
- can be closed with a tight-fitting, puncture-resistant lid, without sharps being able to come out,
- upright and stable during use,
- leak-resistant, and
- properly labeled to warn of hazardous waste inside the container.

When your FDA-cleared sharps disposal container is almost full, you will need to follow your community guidelines for the right way to dispose of FDA-cleared sharps disposal container. There may be state or local laws about how you should throw away used ALTUVIIIO supplies.

Do not dispose of your used FDA-cleared sharps disposal container in your household trash unless your community guidelines permit this.

Do not recycle your used FDA-cleared sharps disposal container.

Keep your FDA-cleared sharps disposal container out of the reach of children.

This Instructions for Use has been approved by the U.S. Food and Drug Administration.

Manufactured by:
Bioverativ Therapeutics Inc.
Waltham, MA 02451
A SANOFI COMPANY
US License Number 2078

©2025 Bioverativ Therapeutics Inc. All rights reserved.

For more information go to www.ALTUVIIIO.com or call 1-800-633-1610

Revised: DEC 2025

PRINCIPAL DISPLAY PANEL - 250 IU Kit Carton

250 IU Nominal

NDC 71104-978-01

ALTUVIIIO™
[Antihemophilic Factor (Recombinant),
Fc-VWF-XTEN Fusion Protein-ehtl]

For Intravenous Use

This package contains:

- (1) Single-dose vial containing lyophilized powder for reconstitution for
  intravenous injection
- (1) Prefilled diluent syringe containing 3 mL sterile water for injection (sWFI) with
  plunger rod
- (1) Sterile vial adapter reconstitution device
- (1) Package Insert

Rx Only

Manufactured by:
Bioverativ Therapeutics Inc.
Waltham, MA 02451

A SANOFI COMPANY
US License Number 2078

www.ALTUVIIIO.com
1-800-633-1610

Diluent origin Germany
Plunger Rod origin France
Vial Adapter origin Israel

sanofi

PRINCIPAL DISPLAY PANEL - 500 IU Kit Carton

500 IU Nominal

NDC 71104-979-01

ALTUVIIIO™
[Antihemophilic Factor (Recombinant),
Fc-VWF-XTEN Fusion Protein-ehtl]

For Intravenous Use

This package contains:

- (1) Single-dose vial containing lyophilized powder for reconstitution for
  intravenous injection
- (1) Prefilled diluent syringe containing 3 mL sterile water for injection (sWFI) with
  plunger rod
- (1) Sterile vial adapter reconstitution device
- (1) Package Insert

Rx Only

Manufactured by:
Bioverativ Therapeutics Inc.
Waltham, MA 02451

A SANOFI COMPANY
US License Number 2078

www.ALTUVIIIO.com
1-800-633-1610

Diluent origin Germany
Plunger Rod origin France
Vial Adapter origin Israel

sanofi

PRINCIPAL DISPLAY PANEL - 1000 IU Kit Carton

1000 IU Nominal

NDC 71104-981-01

ALTUVIIIO™
[Antihemophilic Factor (Recombinant),
Fc-VWF-XTEN Fusion Protein-ehtl]

For Intravenous Use

This package contains:

- (1) Single-dose vial containing lyophilized powder for reconstitution for
  intravenous injection
- (1) Prefilled diluent syringe containing 3 mL sterile water for injection (sWFI) with
  plunger rod
- (1) Sterile vial adapter reconstitution device
- (1) Package Insert

Rx Only

Manufactured by:
Bioverativ Therapeutics Inc.
Waltham, MA 02451

A SANOFI COMPANY
US License Number 2078

www.ALTUVIIIO.com
1-800-633-1610

Diluent origin Germany
Plunger Rod origin France
Vial Adapter origin Israel

sanofi

PRINCIPAL DISPLAY PANEL - 2000 IU Kit Carton

2000 IU Nominal

NDC 71104-982-01

ALTUVIIIO™
[Antihemophilic Factor (Recombinant),
Fc-VWF-XTEN Fusion Protein-ehtl]

For Intravenous Use

This package contains:

- (1) Single-dose vial containing lyophilized powder for reconstitution for
  intravenous injection
- (1) Prefilled diluent syringe containing 3 mL sterile water for injection (sWFI) with
  plunger rod
- (1) Sterile vial adapter reconstitution device
- (1) Package Insert

Rx Only

Manufactured by:
Bioverativ Therapeutics Inc.
Waltham, MA 02451

A SANOFI COMPANY
US License Number 2078

www.ALTUVIIIO.com
1-800-633-1610

Diluent origin Germany
Plunger Rod origin France
Vial Adapter origin Israel

sanofi

PRINCIPAL DISPLAY PANEL - 3000 IU Kit Carton

3000 IU Nominal

NDC 71104-983-01

ALTUVIIIO™
[Antihemophilic Factor (Recombinant),
Fc-VWF-XTEN Fusion Protein-ehtl]

For Intravenous Use

This package contains:

- (1) Single-dose vial containing lyophilized powder for reconstitution for
  intravenous injection
- (1) Prefilled diluent syringe containing 3 mL sterile water for injection (sWFI) with
  plunger rod
- (1) Sterile vial adapter reconstitution device
- (1) Package Insert

Rx Only

Manufactured by:
Bioverativ Therapeutics Inc.
Waltham, MA 02451

A SANOFI COMPANY
US License Number 2078

www.ALTUVIIIO.com
1-800-633-1610

Diluent origin Germany
Plunger Rod origin France
Vial Adapter origin Israel

sanofi

PRINCIPAL DISPLAY PANEL - 4000 IU Kit Carton

4000 IU Nominal

NDC 71104-984-01

ALTUVIIIO™
[Antihemophilic Factor (Recombinant),
Fc-VWF-XTEN Fusion Protein-ehtl]

For Intravenous Use

This package contains:

- (1) Single-dose vial containing lyophilized powder for reconstitution for
  intravenous injection
- (1) Prefilled diluent syringe containing 3 mL sterile water for injection (sWFI) with
  plunger rod
- (1) Sterile vial adapter reconstitution device
- (1) Package Insert

Rx Only

Manufactured by:
Bioverativ Therapeutics Inc.
Waltham, MA 02451

A SANOFI COMPANY
US License Number 2078

www.ALTUVIIIO.com
1-800-633-1610

Diluent origin Germany
Plunger Rod origin France
Vial Adapter origin Israel

sanofi